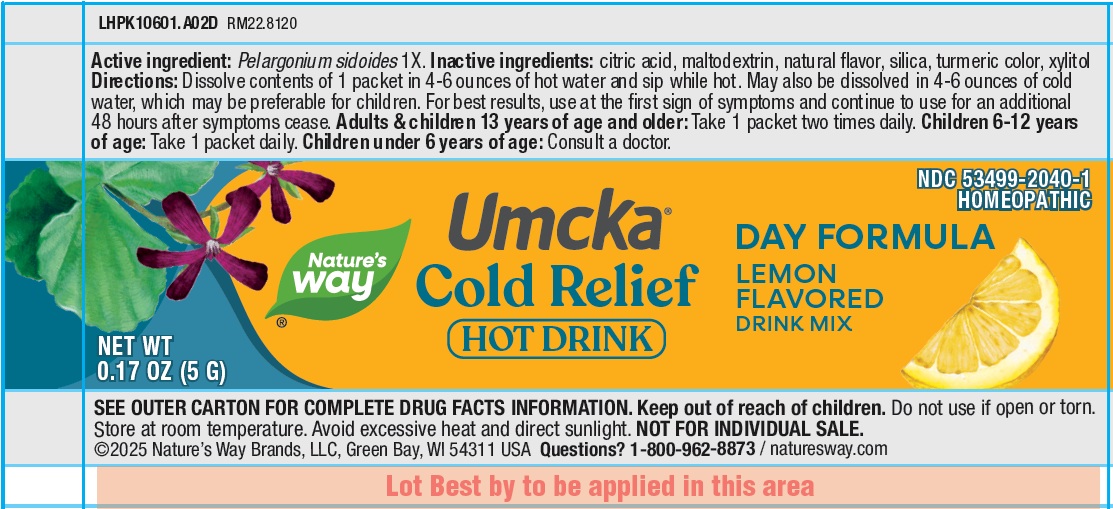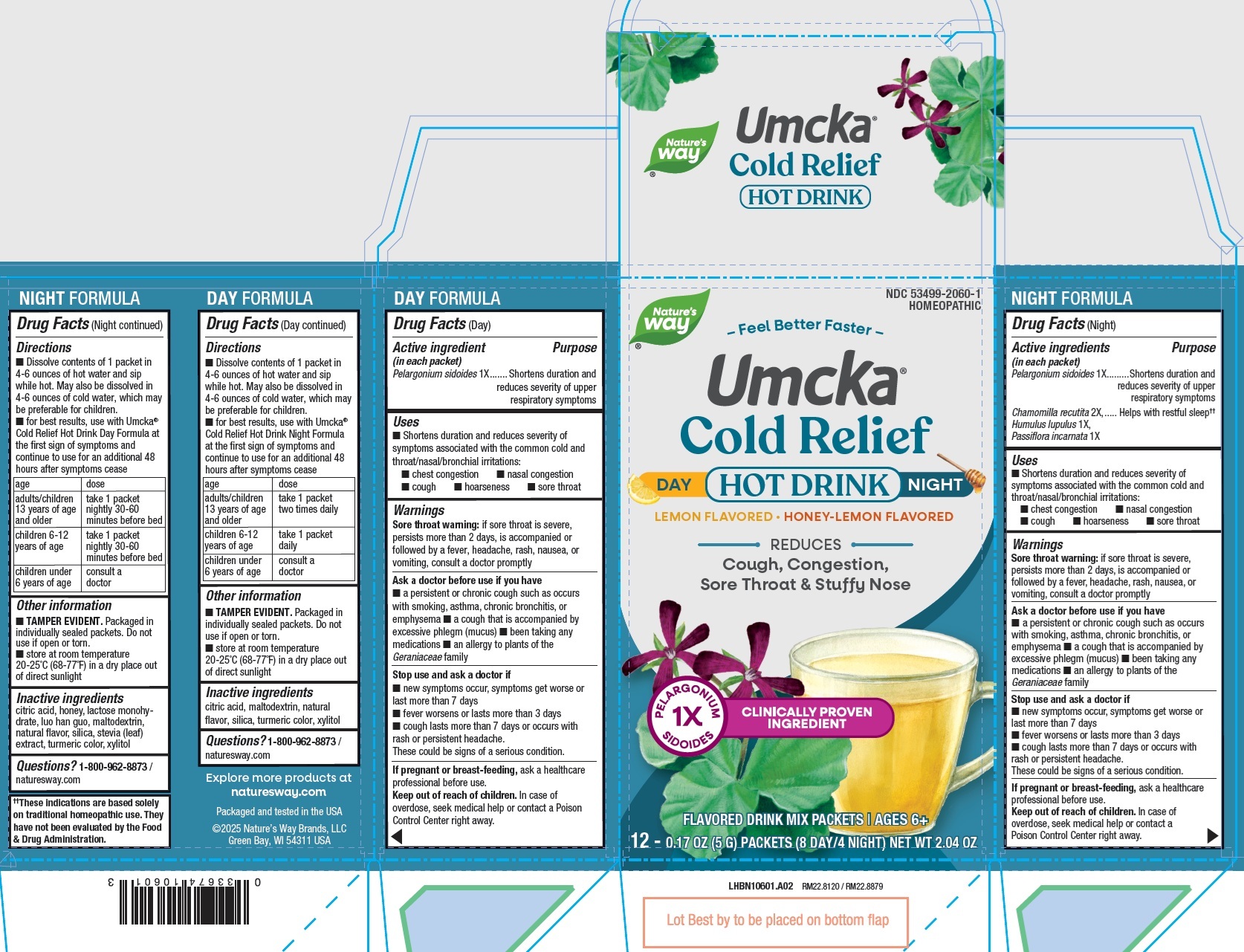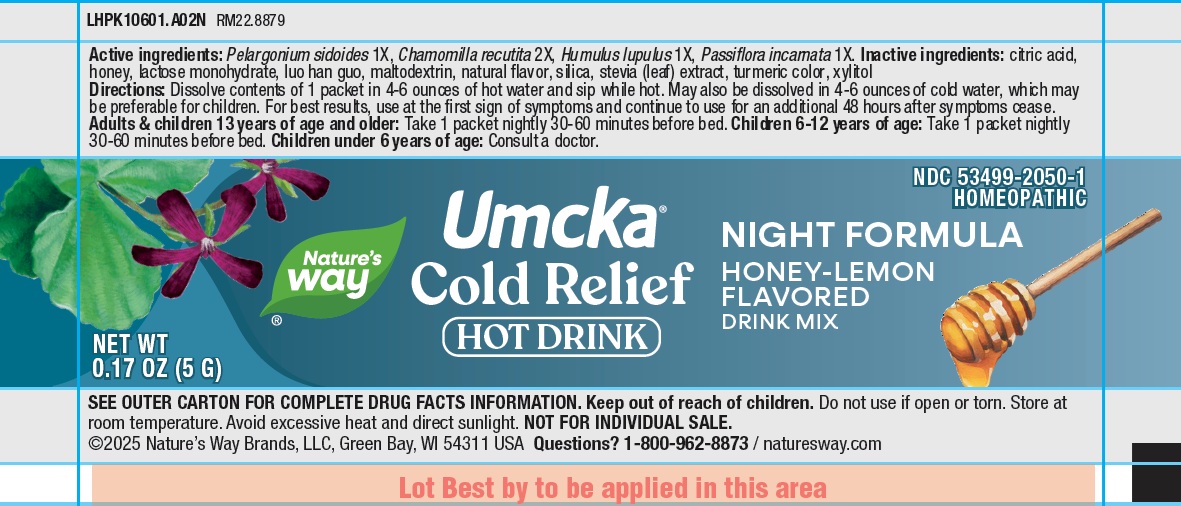 DRUG LABEL: Natures Way Cold Relief Hot Drink
NDC: 80228-2060 | Form: KIT | Route: TOPICAL
Manufacturer: Universal Synergetics, Inc
Category: otc | Type: HUMAN OTC DRUG LABEL
Date: 20250821

ACTIVE INGREDIENTS: PELARGONIUM SIDOIDES WHOLE 1 [hp_X]/1 g; PELARGONIUM SIDOIDES WHOLE 1 [hp_X]/1 g; MATRICARIA CHAMOMILLA ROOT 2 [hp_X]/1 g; HOPS 1 [hp_X]/1 g; PASSIFLORA INCARNATA WHOLE 1 [hp_X]/1 g
INACTIVE INGREDIENTS: CITRIC ACID MONOHYDRATE; MALTODEXTRIN; SILICON DIOXIDE; XYLITOL; CITRIC ACID MONOHYDRATE; HONEY; LACTOSE MONOHYDRATE; SIRAITIA GROSVENORII FRUIT; MALTODEXTRIN; SILICON DIOXIDE; XYLITOL

Nature's Way Cold Relief Hot Drink

Active ingredient (in each packet)

Pelargonium sidoides1X

Purpose

Shortens duration and reduces severity of upper respiratory symptoms

Uses

• Shortens duration and reduces severity of symptoms associated with the common cold and throat/nasal/bronchial irritations:
• chest congestion • nasal congestion • cough • hoarseness • sore throat

Warnings

Sore throat warning:if sore throat is severe, persists more than 2 days, is accompanied or followed by a fever, headache, rash, nausea, or vomiting, consult a doctor promptly

Ask a doctor before use if you have

• a persistent or chronic cough such as occurs with smoking, asthma, chronic bronchitis, or emphysema • a cough that is accompanied by excessive phlegm (mucus) • been taking any medications • an allergy to plants of the Geraniaceae family

Stop use and ask a doctor if

• new symptoms occur, symptoms get worse or last more than 7 days
• fever worsens or lasts more than 3 days
• cough lasts more than 7 days or occurs with rash or persistent headache. These could be signs of a serious condition.

If pregnant or breast-feeding,

ask a healthcare professional before use.

Keep out of reach of children.

In case of overdose, seek medical help or contact a Poison Control Center right away.

Directions

• Dissolve contents of 1 packet in 4-6 ounces of hot water and sip while hot. May also be dissolved in 4-6 ounces of cold water, which may be preferable for children.
• for best results, use with Umcka® Cold Relief Hot Drink Night Formula at the first sign of symptoms and continue to use for an additional 48 hours after symptoms cease

age | dose
adults/children 13 years of age and older | take 1 packet two times daily
children 6-12 years of age | take 1 packet daily
children under 6 years of age | consult a doctor

Other information

• TAMPER EVIDENT. Packaged in individually sealed packets. Do not use if open or torn.
• store at room temperature 20-25°C (68-77°F) in a dry place out of direct sunlight

Inactive ingredients

citric acid, maltodextrin, natural flavor, silica, turmeric color, xylitol

Questions?

1-800-962-8873 / naturesway.com

Active ingredients (in each packet)

Pelargonium sidoides 1X
Chamomilla recutita 2X
Humulus lupulus 1X
Passiflora incarnata 1X

Purpose

Shortens duration and reduces severity of upper respiratory symptoms
Helps with restful sleep††

Uses

•Shortens duration and reduces severity of symptoms associated with the common cold and throat/nasal/bronchial irritations:
• chest congestion • nasal congestion • cough • hoarseness • sore throat

Warnings

Sore throat warning:if sore throat is severe, persists more than 2 days, is accompanied or followed by a fever, headache, rash, nausea, or vomiting, consult a doctor promptly

Ask a doctor before use if you have

• a persistent or chronic cough such as occurs with smoking, asthma, chronic bronchitis, or emphysema • a cough that is accompanied by
excessive phlegm (mucus) • been taking any medications • an allergy to plants of the Geraniaceae family

Stop use and ask a doctor if

• new symptoms occur, symptoms get worse or last more than 7 days
• fever worsens or lasts more than 3 days
• cough lasts more than 7 days or occurs with rash or persistent headache. These could be signs of a serious condition.

If pregnant or breast-feeding,

ask a healthcare professional before use.

Keep out of reach of children.

In case of overdose, seek medical help or contact a Poison Control Center right away.

Directions

• Dissolve contents of 1 packet in 4-6 ounces of hot water and sip while hot. May also be dissolved in 4-6 ounces of cold water, which may be preferable for children.
• for best results, use with Umcka® Cold Relief Hot Drink Day Formula at the first sign of symptoms and continue to use for an additional 48 hours after symptoms cease

age | dose
adults/children 13 years of age and older | take 1 packet nightly 30-60 minutes before bed
children 6-12 years of age | take 1 packet nightly 30-60 minutes before bed
children under 6 years of age | consult a doctor

Other information

• TAMPER EVIDENT. Packaged in individually sealed packets. Do not use if open or torn.
• store at room temperature 20-25°C (68-77°F) in a dry place out of direct sunlight

Inactive ingredients

citric acid, honey, lactose monohydrate, luo han guo, maltodextrin, natural flavor, silica, stevia (leaf) extract, turmeric color, xylitol

Questions?

1-800-962-8873 / naturesway.com